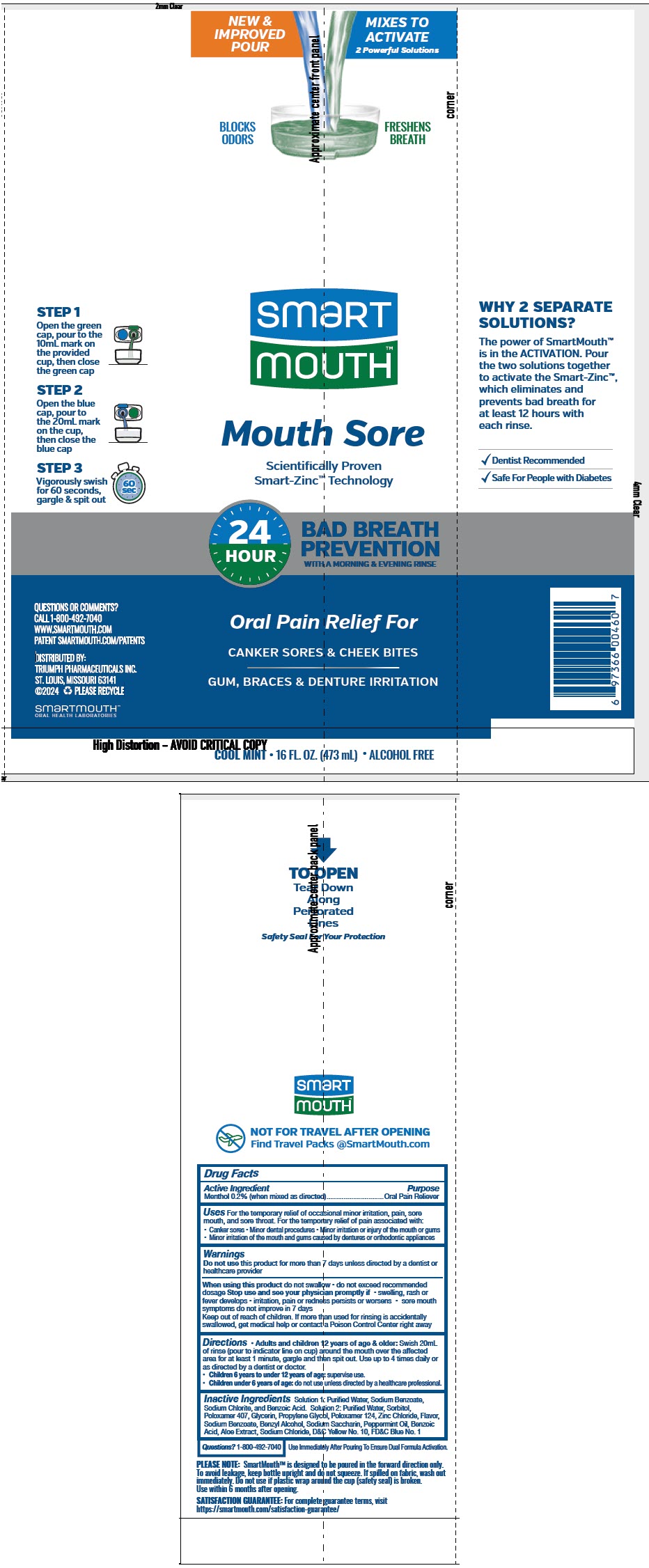 DRUG LABEL: SmartMouth Mouthwash 
NDC: 76357-419 | Form: KIT | Route: DENTAL
Manufacturer: Triumph Pharmaceuticals, Inc.
Category: otc | Type: HUMAN OTC DRUG LABEL
Date: 20241218

ACTIVE INGREDIENTS: MENTHOL, UNSPECIFIED FORM 10 mg/20 mL
INACTIVE INGREDIENTS: Water; Glycerin; Poloxamer 407; Propylene Glycol; Aloe; Poloxamer 124; Zinc Chloride; Sodium; Benzoic Acid; Saccharin Sodium; Sodium Chloride; Benzyl Alcohol; Sorbitol; Peppermint

SmartMouth™ Mouthwash
Mouth Sore Solution 1

Drug Facts

Active Ingredient

Menthol 0.2% (when mixed as directed)

Purpose

Oral Pain Reliever

Uses

For the temporary relief of occasional minor irritation, pain, sore mouth, and sore throat. For the temporary relief of pain associated with:

- Canker sores
- Minor dental procedures
- Minor irritation or injury of the mouth or gums
- Minor irritation of the mouth and gums caused by dentures or orthodontic appliances

Warnings

Do not use this product for more than 7 days unless directed by a dentist or healthcare provider

When using this product do not swallow

- do not exceed recommended dosage

Stop use and see your physician promptly if

- swelling, rash or fever develops
- irritation, pain or redness persists or worsens
- sore mouth symptoms do not improve in 7 days

Keep out of reach of children. If more than used for rinsing is accidentally swallowed, get medical help or contact a Poison Control Center right away

Directions

- Adults and children 12 years of age & older: Swish 20mL of rinse (pour to indicator line on cup) around the mouth over the affected area for at least 1 minute, gargle and then spit out. Use up to 4 times daily or as directed by a dentist or doctor.
- Children 6 years to under 12 years of age: supervise use.
- Children under 6 years of age: do not use unless directed by a healthcare professional.

Inactive Ingredients

Solution 1: Purified Water, Sodium Benzoate, Sodium Chlorite, and Benzoic Acid. Solution 2: Purified Water, Sorbitol, Poloxamer 407, Glycerin, Propylene Glycol, Poloxamer 124, Zinc Chloride, Flavor, Sodium Benzoate, Benzyl Alcohol, Sodium Saccharin, Peppermint Oil, Benzoic Acid, Aloe Extract, Sodium Chloride, D&C Yellow No. 10, FD&C Blue No. 1

Questions?

1-800-492-7040

DISTRIBUTED BY:
TRIUMPH PHARMACEUTICALS INC.
ST. LOUIS, MISSOURI 63141

PRINCIPAL DISPLAY PANEL - Kit Bottle Label

NEW &
IMPROVED
POUR

MIXES TO
ACTIVATE
2 Powerful Solutions

BLOCKS
ODORS

FRESHENS
BREATH

smart
mouth™

Mouth Sore

Scientifically Proven
Smart-Zinc™ Technology

24
HOUR

BAD BREATH
PREVENTION
WITH A MORNING & EVENING RINSE

Oral Pain Relief For

CANKER SORES & CHEEK BITES

GUM, BRACES & DENTURE IRRITATION

COOL MINT • 16 FL. OZ. (473 mL) • ALCOHOL FREE